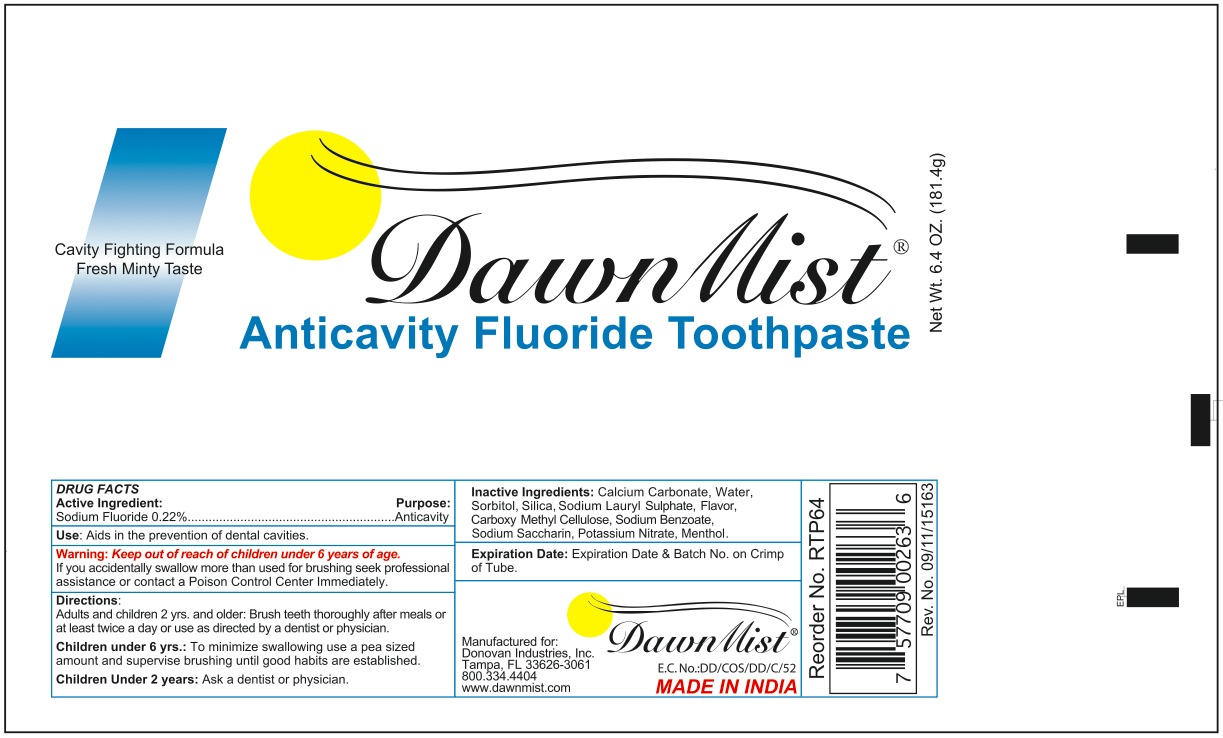 DRUG LABEL: dawnmist
NDC: 55504-4341 | Form: PASTE
Manufacturer: Donavan
Category: otc | Type: HUMAN OTC DRUG LABEL
Date: 20120123

ACTIVE INGREDIENTS: sodium fluoride 39.9 g/181.4 g
INACTIVE INGREDIENTS: CALCIUM CARBONATE; WATER ; SORBITOL ; SODIUM LAURYL SULFATE; SILICON DIOXIDE; CARBOXYMETHYLCELLULOSE  ; PEPPERMINT ; POTASSIUM NITRATE; SODIUM BENZOATE  ; SACCHARIN SODIUM DIHYDRATE ; SODIUM FLUORIDE; MENTHOL

Dawnmist toothpaste

ACTIVE INGREDIENT

sodium fluroide 0.22 % anticavity

INACTIVE INGREDIENT

calcium carbonate, water, sorbitol, silica, sodium lauryl sulphate, flavor, carboxyl methyl cellulose, sodium benzoate, sodium saccharin, potassium nitrate, menthol

DOSAGE AND ADMINISTRATION

adults and children 2 yrs. and older: brush teeth thoroughly after meals or at least twice a day or use as directed by a dentist or physician.

children under 6 yrs.: to minimize swallowing use a pea sized amount and supervise brushing until good habits are established.

children under 2 years: ask a dentist or physician.

INDICATIONS AND USAGE

aids in the prevention of dental cavities.

PURPOSE

aids in the prevention of dental cavities.

keep out of reach of children under 6 years of age. if you accidentally swallow more than used for brushing seek professional assistance or contact a poison control center immediately.

keep out of reach of children under 6 years of age. if you accidentally swallow more than used for brushing seek professional assistance or contact a poison control center immediately.

USER SAFETY WARNINGS

expiration date: expiration date and batch no. on crimp of tube.

PACKAGE LABEL

dawnmist anticavity fluoride toothpaste.